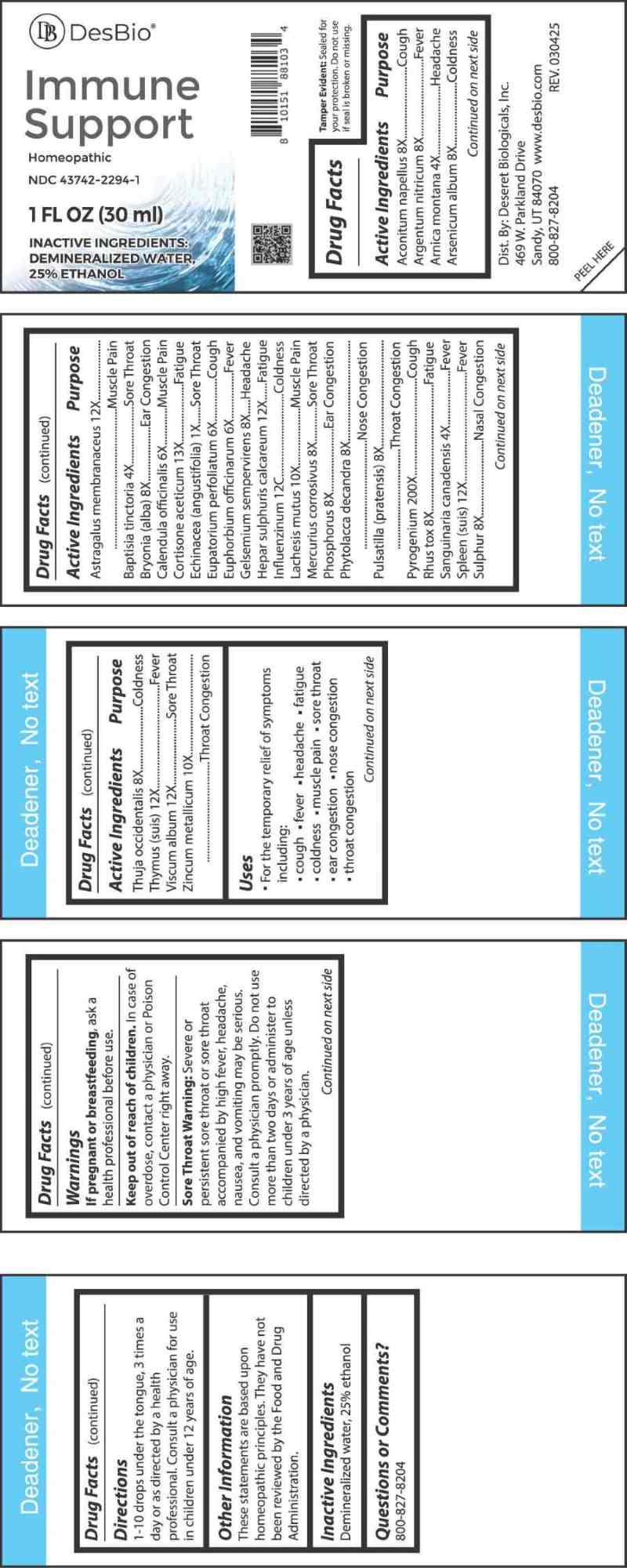 DRUG LABEL: Immune Support
NDC: 43742-2294 | Form: LIQUID
Manufacturer: Deseret Biologicals, Inc.
Category: homeopathic | Type: HUMAN OTC DRUG LABEL
Date: 20260102

ACTIVE INGREDIENTS: ACONITUM NAPELLUS WHOLE 8 [hp_X]/1 mL; SILVER NITRATE 8 [hp_X]/1 mL; ARNICA MONTANA WHOLE 4 [hp_X]/1 mL; ARSENIC TRIOXIDE 8 [hp_X]/1 mL; ASTRAGALUS MONGHOLICUS ROOT 12 [hp_X]/1 mL; BAPTISIA TINCTORIA ROOT 4 [hp_X]/1 mL; BRYONIA ALBA ROOT 8 [hp_X]/1 mL; CALENDULA OFFICINALIS FLOWERING TOP 6 [hp_X]/1 mL; CORTISONE ACETATE 13 [hp_X]/1 mL; ECHINACEA ANGUSTIFOLIA WHOLE 1 [hp_X]/1 mL; EUPATORIUM PERFOLIATUM FLOWERING TOP 6 [hp_X]/1 mL; EUPHORBIA RESINIFERA RESIN 6 [hp_X]/1 mL; GELSEMIUM SEMPERVIRENS ROOT 8 [hp_X]/1 mL; CALCIUM SULFIDE 12 [hp_X]/1 mL; INFLUENZA A VIRUS A/VICTORIA/4897/2022 IVR-238 (H1N1) ANTIGEN (FORMALDEHYDE INACTIVATED) 12 [hp_C]/1 mL; INFLUENZA A VIRUS A/THAILAND/8/2022 IVR-237 (H3N2) ANTIGEN (FORMALDEHYDE INACTIVATED) 12 [hp_C]/1 mL; INFLUENZA B VIRUS B/AUSTRIA/1359417/2021 BVR-26 WHOLE 12 [hp_C]/1 mL; INFLUENZA B VIRUS B/PHUKET/3073/2013 BVR-1B WHOLE 12 [hp_C]/1 mL; LACHESIS MUTA VENOM 10 [hp_X]/1 mL; MERCURIC CHLORIDE 8 [hp_X]/1 mL; PHOSPHORUS 8 [hp_X]/1 mL; PHYTOLACCA AMERICANA ROOT 8 [hp_X]/1 mL; PULSATILLA PRATENSIS WHOLE 8 [hp_X]/1 mL; RANCID BEEF 200 [hp_X]/1 mL; TOXICODENDRON PUBESCENS LEAF 8 [hp_X]/1 mL; SANGUINARIA CANADENSIS ROOT 4 [hp_X]/1 mL; SUS SCROFA SPLEEN 12 [hp_X]/1 mL; SULFUR 8 [hp_X]/1 mL; THUJA OCCIDENTALIS LEAFY TWIG 8 [hp_X]/1 mL; SUS SCROFA THYMUS 12 [hp_X]/1 mL; VISCUM ALBUM FRUITING TOP 12 [hp_X]/1 mL; ZINC 10 [hp_X]/1 mL
INACTIVE INGREDIENTS: WATER; ALCOHOL

DRUG FACTS:

ACTIVE INGREDIENTS:

Aconitum Napellus 8X, Argentum Nitricum 8X, Arnica Montana 4X, Arsenicum Album 8X, Astragalus Membranaceus 12X, Baptisia Tinctoria 4X, Bryonia (Alba) 8X, Calendula Officinalis 6X, Cortisone Aceticum 13X, Echinacea (Angustifolia) 1X, Eupatorium Perfoliatum 6X, Euphorbium Officinalis 6X, Gelsemium Sempervirens 8X, Hepar Sulphuris Calcareum 12X, Influenzinum 12C , Lachesis Mutus 10X, Mercurius Corrosivus 8X, Phosphorus 8X, Phytolacca Decandra 8X, Pulsatilla (Pratensis) 8X, Pyrogenium 200X, Rhus Tox 8X, Sanguinaria Canadensis 4X, Spleen (Suis) 12X, Sulphur 8X, Thuja Occidentalis 8X, Thymus (Suis) 12X, Viscum Album 12X, Zincum Metallicum 10X.

PURPOSE:

Aconitum Napellus - Cough, Argentum Nitricum -Fever, Arnica Montana - Headache, Arsenicum Album - Coldness, Astragalus Membranaceus – Muscle Pain, Baptisia Tinctoria – Sore Throat, Bryonia (Alba) – Ear Congestion, Calendula Officinalis – Muscle Pain, Cortisone Aceticum - Fatigue, Echinacea (Angustifolia) – Sore Throat, Eupatorium Perfoliatum - Cough, Euphorbium Officinalis - Fever, Gelsemium Sempervirens - Headache, Hepar Sulphuris Calcareum - Fatigue, Influenzinum - Coldness , Lachesis Mutus – Muscle Pain, Mercurius Corrosivus – Sore Throat, Phosphorus – Ear Congestion, Phytolacca Decandra – Nose Congestion, Pulsatilla (Pratensis) – Throat Congestion, Pyrogenium - Cough, Rhus Tox - Fatigue, Sanguinaria Canadensis - Fever, Spleen (Suis) - Fever, Sulphur – Nasal Congestion, Thuja Occidentalis - Coldness, Thymus (Suis) - Fever, Viscum Album – Sore Throat, Zincum Metallicum – Throat Congestion

USES:

• For the temporary relief of symptoms including:

• cough • fever • headache • fatigue • coldness • muscle pain • sore throat • ear congestion • nose congestion • throat congestion.

These statements are based upon homeopathic principles. They have not been reviewed by the Food and Drug Administration.

WARNINGS:

If pregnant or breastfeeding, ask a health professional before use.

Keep out of reach of children. In case of overdose, contact a physician or Poison Control Center right away.

Sore Throat Warning: Severe or persistent sore throat or sore throat accompanied by high fever, headache, nausea, and vomiting may be serious. Consult a physician promptly. Do not use more than two days or administer to children under 3 years of age unless directed by a physician.

Tamper Evident: Sealed for your protection. Do not use if seal is broken or missing.

KEEP OUT OF REACH OF CHILDREN:

In case of overdose, contact physician or a Poison Control Center right away.

DIRECTIONS:

1-10 drops under the tongue, 3 times a day or as directed by a health professional. Consult a physician for use in children under 12 years of age.

INACTIVE INGREDIENTS:

Demineralized water, 25% ethanol

QUESTIONS:

Dist. By: Deseret Biologicals, Inc.
469 W. Parkland Drive
Sandy, UT 84070

www.desbio.com

800-827-8204

PACKAGE LABEL DISPLAY:

DesBio
Immune Support
Homeopathic
NDC 43742-2294-1
1 FL OZ (30 ml)